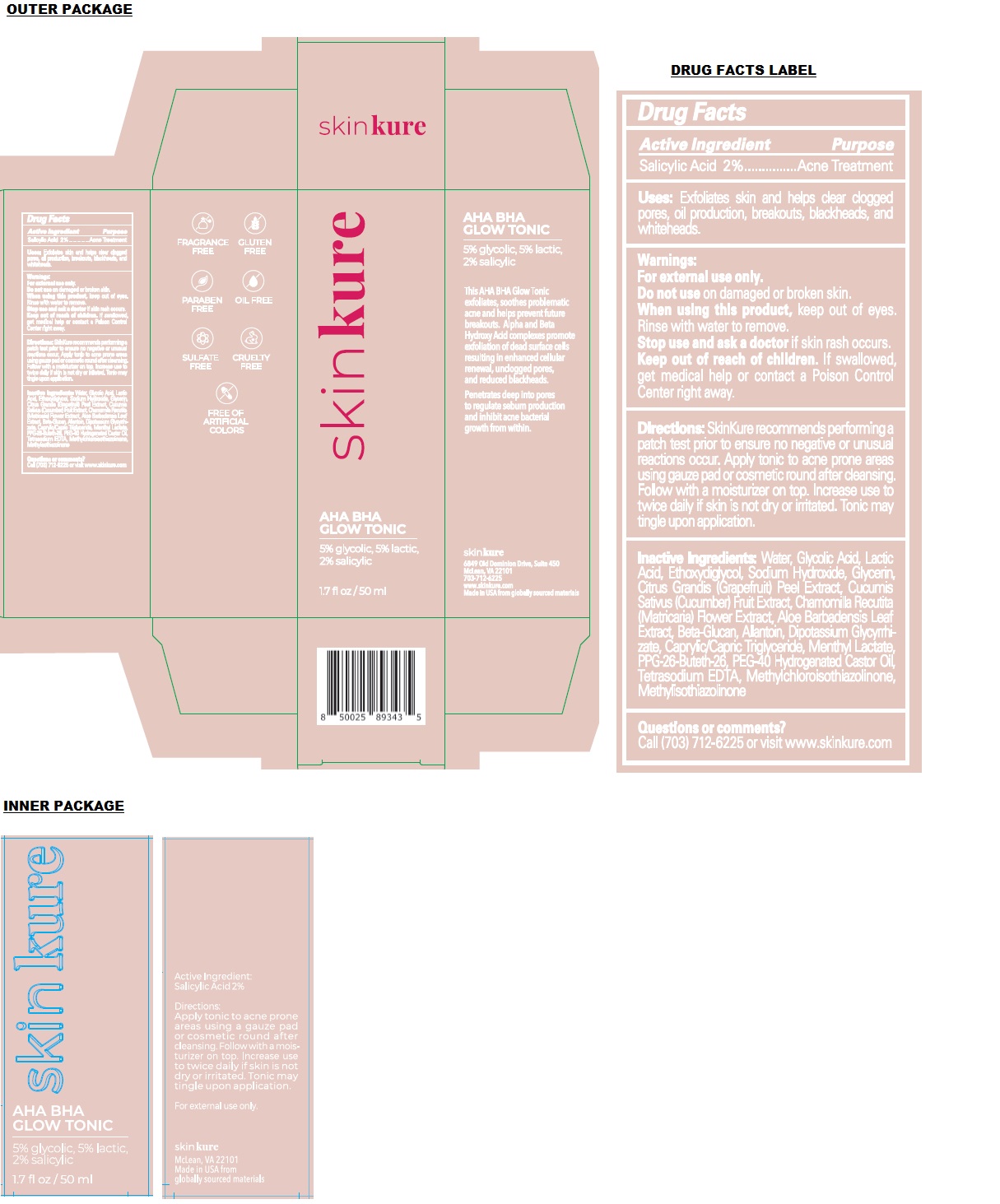 DRUG LABEL: AHA BHA GLOW TONIC
NDC: 83865-001 | Form: LIQUID
Manufacturer: Skinkure
Category: otc | Type: HUMAN OTC DRUG LABEL
Date: 20240206

ACTIVE INGREDIENTS: SALICYLIC ACID 2 g/100 mL
INACTIVE INGREDIENTS: WATER; GLYCOLIC ACID; LACTIC ACID, UNSPECIFIED FORM; DIETHYLENE GLYCOL MONOETHYL ETHER; SODIUM HYDROXIDE; GLYCERIN; CITRUS MAXIMA FRUIT RIND; CUCUMBER; CHAMOMILE; ALOE VERA LEAF; YEAST .BETA.-D-GLUCAN; ALLANTOIN; GLYCYRRHIZINATE DIPOTASSIUM; MEDIUM-CHAIN TRIGLYCERIDES; MENTHYL LACTATE, (-)-; PPG-26-BUTETH-26; POLYOXYL 40 HYDROGENATED CASTOR OIL; EDETATE SODIUM; METHYLCHLOROISOTHIAZOLINONE; METHYLISOTHIAZOLINONE

AHA BHA GLOW TONIC

Active Ingredient

Salicylic Acid 2%

Purpose

Acne Treatment

Uses:

Exfoliates skin and helps clear clogged pores, oil production, breakouts, blackheads, and whiteheads.

Warnings:

For external use only.

Do not use on damaged or broken skin.

When using this product, keep out of eyes. Rinse with water to remove.

Stop use and ask a doctor if skin rash occurs.

Keep out of reach of children. If swallowed, get medical help or contact a Poison Control Center right away.

Directions:

SkinKure recommends performing a patch test prior to ensure no negative or unusual reactions occur. Apply tonic to acne prone areas using gauze pad or cosmetic round after cleansing. Follow with a moisturizer on top. Increase use to twice daily if skin is not dry or irritated. Tonic may tingle upon application.

Inactive Ingredients:

Water, Glycolic Acid, Lactic Acid, Ethoxydiglycol, Sodium Hydroxide, Glycerin, Citrus Grandis (Grapefruit) Peel Extract, Cucumis Sativus (Cucumber) Fruit Extract, Chamomilla Recutita (Matricaria) Flower Extract, Aloe Barbadensis Leaf Extract, Beta-Glucan, Allantoin, Dipotassium Glycyrrhizate, Caprylic/Capric Triglyceride, Menthyl Lactate, PPG-26-Buteth-26, PEG-40 Hydrogenated Castor Oil, Tetrasodium EDTA, Methylchloroisothiazolinone, Methylisothiazolinone

Questions or comments?

Call (703) 712-6225 or visit www.skinkure.com

5% glycolic, 5% lactic, 2% salicylic

This AHA BHA Glow Tonic exfoliates, soothes problematic acne and helps prevent future breakouts. Alpha and Beta Hydroxy Acid complexes promote exfoliation of dead surface cells resulting in enhanced cellular renewal, unclogged pores, and reduced blackheads.

Penetrates deep into pores to regulate sebum production and inhibit acne bacterial growth from within.

skinkure
6849 Old Dominion Drive, Suite 450
McLean, VA 22101
703-712-6225
www.skinkure.com
Made in USA from globally sourced materials

FRAGRANCE FREE

GLUTEN FREE

PARABEN FREE

OIL FREE

SULFATE FREE

CRUELTY FREE

FREE OF ARTIFICIAL COLORS